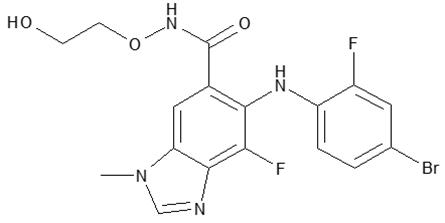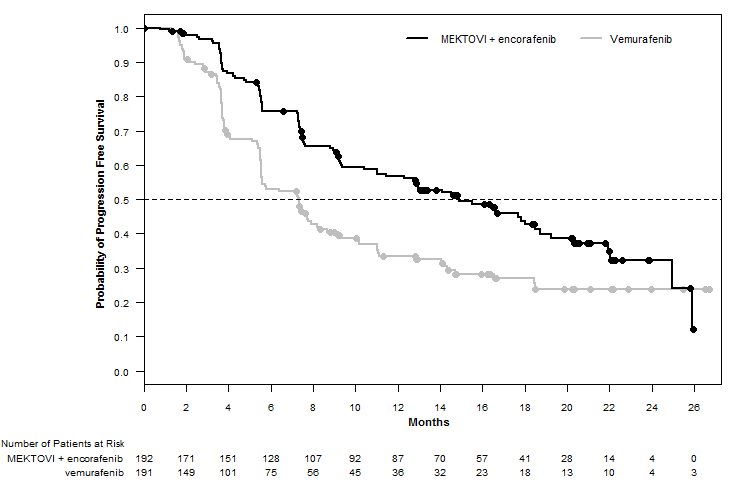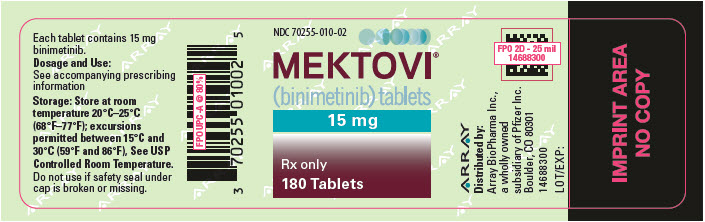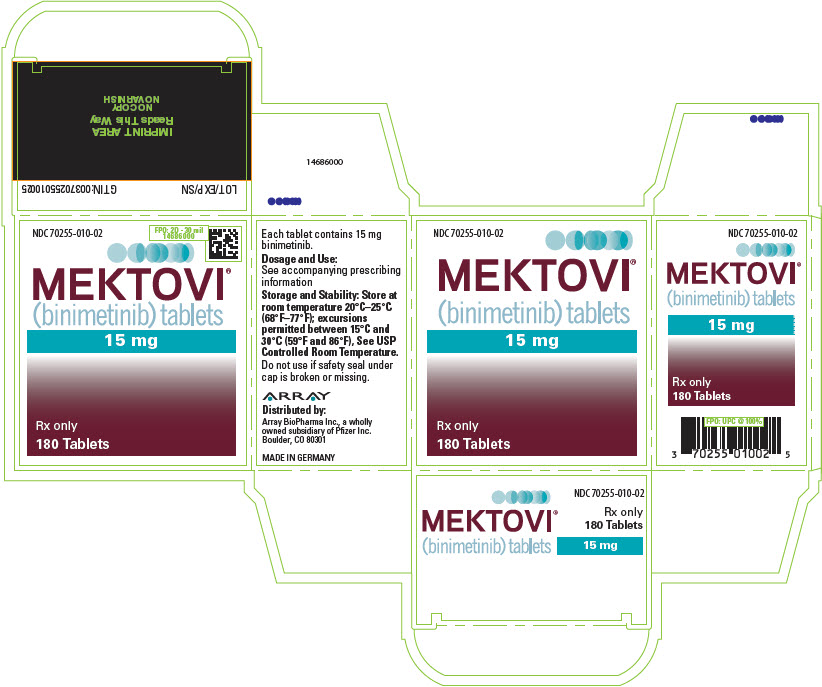 DRUG LABEL: MEKTOVI
NDC: 70255-010 | Form: TABLET, FILM COATED
Manufacturer: Array BioPharma Inc.
Category: prescription | Type: HUMAN PRESCRIPTION DRUG LABEL
Date: 20250320

ACTIVE INGREDIENTS: BINIMETINIB 15 mg/1 1
INACTIVE INGREDIENTS: LACTOSE MONOHYDRATE; MICROCRYSTALLINE CELLULOSE; CROSCARMELLOSE SODIUM; MAGNESIUM STEARATE; SILICON DIOXIDE; POLYVINYL ALCOHOL, UNSPECIFIED; POLYETHYLENE GLYCOL 3350; TITANIUM DIOXIDE; TALC; FERRIC OXIDE YELLOW; FERROSOFERRIC OXIDE

HIGHLIGHTS OF PRESCRIBING INFORMATION

These highlights do not include all the information needed to use MEKTOVI safely and effectively. See full prescribing information for MEKTOVI.
MEKTOVI® (binimetinib) tablets, for oral use
Initial U.S. Approval: 2018

1 INDICATIONS AND USAGE

MEKTOVI is a kinase inhibitor indicated:

- in combination with encorafenib, for the treatment of patients with unresectable or metastatic melanoma with a BRAF V600E or V600K mutation, as detected by an FDA-approved test. (1.1, 2.1)
- in combination with encorafenib, for the treatment of adult patients with metastatic non-small cell lung cancer (NSCLC) with a BRAF V600E mutation, as detected by an FDA-approved test. (1.2, 2.1)

2 DOSAGE AND ADMINISTRATION

Melanoma

- Confirm the presence of BRAF V600E or V600K mutation in tumor specimens prior to the initiation of MEKTOVI. (2.1)
- The recommended dose is 45 mg orally twice daily in combination with encorafenib. Take MEKTOVI with or without food. (2.2)
- For patients with moderate or severe hepatic impairment the recommended dose is 30 mg orally twice daily. (2.4, 8.6)

NSCLC

- Confirm the presence of BRAF V600E mutation in tumor or plasma specimens prior to initiating MEKTOVI. (2.1)
- The recommended dose is 45 mg orally twice daily in combination with encorafenib. Take MEKTOVI with or without food. (2.2)

3 DOSAGE FORMS AND STRENGTHS

Tablets: 15 mg. (3)

4 CONTRAINDICATIONS

None. (4)

5 WARNINGS AND PRECAUTIONS

- New Primary Malignancies, Cutaneous and Non-cutaneous: Can occur when MEKTOVI is used in combination with encorafenib. Monitor patients for new malignancies prior to initiation of treatment, during treatment, and after discontinuation of treatment. (5.1)
- Cardiomyopathy: Assess left ventricular ejection fraction (LVEF) before initiating treatment, after one month of treatment, then every 2 to 3 months thereafter. The safety of MEKTOVI has not been established in patients with LVEF below 50%. (5.2)
- Venous Thromboembolism: Deep vein thrombosis and pulmonary embolism can occur. (5.3)
- Ocular Toxicities: Serous retinopathy, retinal vein occlusion (RVO) and uveitis have occurred. Perform an ophthalmologic evaluation at regular intervals and for any visual disturbances. (5.4)
- Interstitial Lung Disease (ILD): Assess new or progressive unexplained pulmonary symptoms or findings for possible ILD. (5.5)
- Hepatotoxicity: Monitor liver function tests before and during treatment with MEKTOVI and encorafenib and as clinically indicated. (5.6)
- Rhabdomyolysis: Monitor creatine phosphokinase and creatinine periodically and as clinically indicated. (5.7)
- Hemorrhage: Major hemorrhagic events can occur in patients receiving MEKTOVI and encorafenib. (5.8)
- Embryo-Fetal Toxicity: Can cause fetal harm. Advise females with reproductive potential of potential risk to the fetus and to use effective contraception. (5.9, 8.1, 8.3)

6 ADVERSE REACTIONS

Melanoma: Most common adverse reactions (≥25%) for MEKTOVI, in combination with encorafenib, are fatigue, nausea, diarrhea, vomiting, and abdominal pain. (6.1)

NSCLC: Most common adverse reactions (≥25%) for MEKTOVI, in combination with encorafenib, are fatigue, nausea, diarrhea, musculoskeletal pain, vomiting, abdominal pain, visual impairment, constipation, dyspnea, rash, and cough. (6.1)

To report SUSPECTED ADVERSE REACTIONS, contact Pfizer Inc. at 1-800-438-1985 or FDA at 1-800-FDA-1088 or www.fda.gov/medwatch.

8 USE IN SPECIFIC POPULATIONS

Lactation: Advise not to breastfeed. (8.2)

FULL PRESCRIBING INFORMATION

1 INDICATIONS AND USAGE

1.1 BRAF V600E or V600K Mutation-Positive Unresectable or Metastatic Melanoma

MEKTOVI is indicated, in combination with encorafenib, for the treatment of patients with unresectable or metastatic melanoma with a BRAF V600E or V600K mutation, as detected by an FDA-approved test [see Dosage and Administration (2.1)].

1.2 BRAF V600E Mutation-Positive Metastatic Non-Small Cell Lung Cancer (NSCLC)

MEKTOVI is indicated, in combination with encorafenib, for the treatment of adult patients with metastatic non-small cell lung cancer (NSCLC) with a BRAF V600E mutation, as detected by an FDA-approved test. [see Dosage and Administration (2.1)].

2 DOSAGE AND ADMINISTRATION

2.1 Patient Selection

BRAF V600E or V600K Mutation-Positive Unresectable or Metastatic Melanoma

Confirm the presence of a BRAF V600E or V600K mutation in tumor specimens prior to initiating MEKTOVI [see Clinical Studies (14)]. Information on FDA-approved tests for the detection of BRAF V600E and V600K mutations in melanoma is available at: http://www.fda.gov/CompanionDiagnostics.

BRAF V600E Mutation-Positive Metastatic Non-Small Cell Lung Cancer (NSCLC)

Confirm the presence of a BRAF V600E mutation in tumor or plasma specimens prior to initiating MEKTOVI [see Clinical Studies (14.2)]. If no mutation is detected in a plasma specimen, test tumor tissue. Information on FDA-approved tests for the detection of BRAF V600E mutations in NSCLC is available at: http://www.fda.gov/CompanionDiagnostics.

2.2 Recommended Dosage and Administration

The recommended dosage of MEKTOVI is 45 mg orally taken twice daily, approximately 12 hours apart, in combination with encorafenib until disease progression or unacceptable toxicity. Refer to the encorafenib prescribing information for recommended encorafenib dosing information.

MEKTOVI may be taken with or without food [see Clinical Pharmacology (12.3)]. Do not take a missed dose of MEKTOVI within 6 hours of the next dose of MEKTOVI.

Do not take an additional dose if vomiting occurs after MEKTOVI administration but continue with the next scheduled dose.

2.3 Dosage Modifications for Adverse Reactions

If encorafenib is permanently discontinued, discontinue MEKTOVI.

Dose reductions for adverse reactions associated with MEKTOVI are presented in Table 1.

Table 1: Recommended Dose Reductions for MEKTOVI for Adverse Reactions
Action | Recommended Dose
First Dose Reduction | 30 mg orally twice daily
Subsequent Modification | Permanently discontinue if unable to tolerate MEKTOVI 30 mg orally twice daily

Dosage modifications for adverse reactions associated with MEKTOVI are presented in Table 2.

Table 2: Recommended Dosage Modifications for MEKTOVI for Adverse Reactions
Severity of Adverse Reaction [National Cancer Institute Common Terminology Criteria for Adverse Events (NCI CTCAE) version 4.03.] | Dose Modification for MEKTOVI
Cardiomyopathy [see Warnings and Precautions (5.2)]
- Asymptomatic, absolute decrease in LVEF of greater than 10% from baseline that is also below lower limit of normal (LLN) | Withhold MEKTOVI for up to 4 weeks, evaluate LVEF every 2 weeks. Resume MEKTOVI at a reduced dose if the following are present:; - LVEF is at or above the lower limit of normal and - Absolute decrease from baseline is 10% or less and - Patient is asymptomatic.; If the LVEF does not recover within 4 weeks permanently discontinue MEKTOVI.
- Symptomatic congestive heart failure or absolute decrease in LVEF of greater than 20% from baseline that is also below LLN | Permanently discontinue MEKTOVI.
Venous Thromboembolism [see Warnings and Precautions (5.3)]
- Uncomplicated deep venous thrombosis (DVT) or pulmonary embolism (PE) | Withhold MEKTOVI.; - If improves to Grade 0-1, resume at a reduced dose. - If no improvement, permanently discontinue MEKTOVI.
- Life threatening PE | Permanently discontinue MEKTOVI.
Serous Retinopathy [see Warnings and Precautions (5.4)]
- Symptomatic serous retinopathy/Retinal pigment epithelial detachments | Withhold MEKTOVI for up to 10 days.; - If improves and becomes asymptomatic, resume at same dose. - If not improved, resume at a lower dose level or permanently discontinue MEKTOVI.
Retinal Vein Occlusion (RVO) [see Warnings and Precautions (5.4)]
- Any Grade | Permanently discontinue MEKTOVI.
Uveitis [see Warnings and Precautions (5.4)]
- Grade 1-3 | If Grade 1 or 2 does not respond to specific ocular therapy, or for Grade 3 uveitis, withhold MEKTOVI for up to 6 weeks.; - If improved, resume at same or reduced dose. - If not improved, permanently discontinue MEKTOVI.
- Grade 4 | Permanently discontinue MEKTOVI.
Interstitial Lung Disease [see Warnings and Precautions (5.5)]
- Grade 2 | Withhold MEKTOVI for up to 4 weeks.; - If improved to Grade 0-1, resume at a reduced dose. - If not resolved within 4 weeks, permanently discontinue MEKTOVI.
- Grade 3 or Grade 4 | Permanently discontinue MEKTOVI.
Hepatotoxicity [see Warnings and Precautions (5.6)]
- Grade 2 AST or ALT increased | Maintain MEKTOVI dose.; - If no improvement within 2 weeks, withhold MEKTOVI until improved to Grade 0-1 or to pretreatment/baseline levels and then resume at the same dose.
- Grade 3 or 4 AST or ALT increased | See Other Adverse Reactions.
Rhabdomyolysis or Creatine Phosphokinase (CPK) elevations [see Warnings and Precautions (5.7)]
- Grade 4 asymptomatic CPK elevation or - Any Grade CPK elevation with symptoms or with renal impairment | Withhold MEKTOVI dose for up to 4 weeks.; - If improved to Grade 0-1 resume at a reduced dose. - If not resolved within 4 weeks, permanently discontinue MEKTOVI.
Dermatologic [other than palmar plantar erythrodysesthesia syndrome (PPES)] [see Adverse Reactions (6.1)]
- Grade 2 | If no improvement within 2 weeks, withhold MEKTOVI until Grade 0-1. Resume at same dose if first occurrence or reduce dose if recurrent.
- Grade 3 | Withhold MEKTOVI until Grade 0-1. Resume at same dose if first occurrence or reduce dose if recurrent.
- Grade 4 | Permanently discontinue MEKTOVI.
Other Adverse Reactions (including Hemorrhage) [see Warnings and Precautions (5.8), Adverse Reactions (6.1)] [Dose modification of MEKTOVI when administered with encorafenib is not recommended for the following adverse reactions: palmar-plantar erythrodysesthesia syndrome (PPES), non-cutaneous RAS mutation-positive malignancies, and QTc prolongation.]
- Recurrent Grade 2 or - First occurrence of any Grade 3 | Withhold MEKTOVI for up to 4 weeks.; - If improves to Grade 0-1 or to pretreatment/baseline levels, resume at reduced dose. - If no improvement, permanently discontinue MEKTOVI.
- First occurrence of any Grade 4 | Permanently discontinue MEKTOVI, or Withhold MEKTOVI for up to 4 weeks.; - If improves to Grade 0-1 or to pretreatment/baseline levels, then resume at a reduced dose. - If no improvement, permanently discontinue MEKTOVI.
- Recurrent Grade 3 | Consider permanently discontinuing MEKTOVI.
- Recurrent Grade 4 | Permanently discontinue MEKTOVI.

Refer to the encorafenib prescribing information for dose modifications for adverse reactions associated with encorafenib.

2.4 Dosage Modifications for Moderate or Severe Hepatic Impairment

For patients with moderate (total bilirubin greater than 1.5 and less than or equal to 3 × ULN and any AST) or severe (total bilirubin levels greater than 3 × ULN and any AST) hepatic impairment, the recommended dosage is 30 mg orally taken twice daily [see Use in Specific Populations (8.6), Clinical Pharmacology (12.3)].

3 DOSAGE FORMS AND STRENGTHS

Tablets: 15 mg, yellow/dark yellow, unscored biconvex oval film-coated tablets debossed with a stylized "A" on one side and "15" on the other side.

4 CONTRAINDICATIONS

None.

5 WARNINGS AND PRECAUTIONS

5.1 New Primary Malignancies

New primary malignancies, cutaneous and non-cutaneous, can occur when MEKTOVI is used in combination with encorafenib.

In PHAROS, cutaneous squamous cell carcinoma and skin papilloma each occurred in 2% of patients who received MEKTOVI in combination with encorafenib.

Monitor patients for new malignancies prior to initiation of treatment, while on treatment, and after discontinuation of treatment [see Dosage and Administration (2.3)].

5.2 Cardiomyopathy

Cardiomyopathy, manifesting as left ventricular dysfunction associated with symptomatic or asymptomatic decreases in ejection fraction, has been reported in patients treated with MEKTOVI in combination with encorafenib. In COLUMBUS, evidence of cardiomyopathy (decrease in LVEF below the institutional LLN with an absolute decrease in LVEF ≥10% below baseline as detected by echocardiography or MUGA) occurred in 7% of patients receiving MEKTOVI plus encorafenib. Grade 3 left ventricular dysfunction occurred in 1.6% of patients. The median time to first occurrence of left ventricular dysfunction (any grade) in patients receiving MEKTOVI in combination with encorafenib was 3.6 months (range 0 to 21 months). Cardiomyopathy resolved in 87% of patients receiving MEKTOVI plus encorafenib.

In PHAROS, evidence of cardiomyopathy (decrease in LVEF below the institutional LLN with an absolute decrease in LVEF ≥10% below baseline as detected by echocardiography or MUGA) occurred in 11% of patients receiving MEKTOVI in combination with encorafenib. Grade 3 left ventricular dysfunction occurred in 1% of patients. Cardiomyopathy resolved in 82% of patients receiving MEKTOVI plus encorafenib.

Assess ejection fraction by echocardiogram or MUGA scan prior to initiating treatment, one month after initiating treatment, and then every 2 to 3 months during treatment. The safety of MEKTOVI in combination with encorafenib has not been established in patients with a baseline ejection fraction that is either below 50% or below the institutional lower limit of normal (LLN). Patients with cardiovascular risk factors should be monitored closely when treated with MEKTOVI.

Withhold, reduce dose, or permanently discontinue based on severity of adverse reaction [see Dosage and Administration (2.3), Adverse Reactions (6.1)].

5.3 Venous Thromboembolism

In COLUMBUS, venous thromboembolism (VTE) occurred in 6% of patients receiving MEKTOVI in combination with encorafenib, including 3.1% of patients who developed pulmonary embolism. In PHAROS, VTE occurred in 7% of patients receiving MEKTOVI in combination with encorafenib, including 1% of patients who developed pulmonary embolism.

Withhold, reduce dose, or permanently discontinue based on severity of adverse reaction [see Dosage and Administration (2.3), Adverse Reactions (6.1)].

5.4 Ocular Toxicities

Serous Retinopathy

In COLUMBUS, serous retinopathy occurred in 20% of patients treated with MEKTOVI in combination with encorafenib; 8% were retinal detachment and 6% were macular edema. Symptomatic serous retinopathy occurred in 8% of patients with no cases of blindness. No patient discontinued MEKTOVI due to serous retinopathy; 6% of patients required dose interruptions or dose reductions. The median time to onset of the first event of serous retinopathy (all grades) was 1.2 months (range 0 to 17.5 months).

In PHAROS, serous retinopathy (retinal detachment) occurred in 2% of patients with no cases of blindness treated with MEKTOVI in combination with encorafenib. No patient permanently discontinued MEKTOVI due to serous retinopathy; 1% of patients required dose interruptions.

Assess for visual symptoms at each visit. Perform an ophthalmologic examination at regular intervals, for new or worsening visual disturbances, and to follow new or persistent ophthalmologic findings. Withhold, reduce dose, or permanently discontinue based on severity of adverse reaction [see Dosage and Administration (2.3), Adverse Reactions (6.1)].

Retinal Vein Occlusion

RVO is a known class-related adverse reaction of MEK inhibitors and may occur in patients treated with MEKTOVI in combination with encorafenib. In patients with BRAF mutation-positive melanoma receiving MEKTOVI with encorafenib (n=690), 1 patient experienced RVO (0.1%).

The safety of MEKTOVI has not been established in patients with a history of RVO or current risk factors for RVO including uncontrolled glaucoma or a history of hyperviscosity or hypercoagulability syndromes.

Perform ophthalmologic evaluation for patient-reported acute vision loss or other visual disturbance within 24 hours. Permanently discontinue MEKTOVI in patients with documented RVO [see Dosage and Administration (2.3), Adverse Reactions (6.1)].

Uveitis

Uveitis, including iritis and iridocyclitis, has been reported in patients treated with MEKTOVI in combination with encorafenib. In COLUMBUS, the incidence of uveitis among patients treated with MEKTOVI in combination with encorafenib was 4%. In PHAROS, uveitis occurred in 1% of patients receiving MEKTOVI in combination with encorafenib.

Assess for visual symptoms at each visit. Perform an ophthalmologic evaluation at regular intervals and for new or worsening visual disturbances, and to follow new or persistent ophthalmologic findings. Withhold, reduce dose, or permanently discontinue based on severity of adverse reaction [see Dosage and Administration (2.3), Adverse Reactions (6.1)].

5.5 Interstitial Lung Disease

In patients with BRAF mutation-positive melanoma receiving MEKTOVI with encorafenib (n=690), 2 patients (0.3%) developed interstitial lung disease (ILD), including pneumonitis. In PHAROS, 1 patient (1%) receiving MEKTOVI with encorafenib developed pneumonitis.

Assess new or progressive unexplained pulmonary symptoms or findings for possible ILD. Withhold, reduce dose, or permanently discontinue based on severity of adverse reaction [see Dosage and Administration (2.3), Adverse Reactions (6.1)].

5.6 Hepatotoxicity

Hepatotoxicity can occur when MEKTOVI is administered in combination with encorafenib. In COLUMBUS, the incidence of Grade 3 or 4 increases in liver function laboratory tests in patients receiving MEKTOVI in combination with encorafenib was 6% for alanine aminotransferase (ALT), 2.6% for aspartate aminotransferase (AST), and 0.5% for alkaline phosphatase. No patient experienced Grade 3 or 4 serum bilirubin elevation. In PHAROS, the incidence of Grade 3 or 4 increases in liver function laboratory tests in patients receiving MEKTOVI in combination with encorafenib was 10% for AST, 9% for ALT, and 3.2% for alkaline phosphatase.

Monitor liver laboratory tests before initiation of MEKTOVI, monthly during treatment, and as clinically indicated. Withhold, reduce dose, or permanently discontinue based on severity of adverse reaction [see Dosage and Administration (2.3), Adverse Reactions (6.1)].

5.7 Rhabdomyolysis

Rhabdomyolysis can occur when MEKTOVI is administered in combination with encorafenib. In COLUMBUS, elevation of laboratory values of serum CPK occurred in 58% of patients treated with MEKTOVI in combination with encorafenib. In patients with BRAF mutation-positive melanoma receiving MEKTOVI with encorafenib (n=690), rhabdomyolysis was reported in 1 patient (0.1%). In PHAROS, elevation of laboratory values of serum creatine kinase (CK) occurred in 41% of patients treated with MEKTOVI in combination with encorafenib. No patient experienced rhabdomyolysis.

Monitor CPK and creatinine levels prior to initiating MEKTOVI, periodically during treatment, and as clinically indicated. Withhold, reduce dose, or permanently discontinue based on severity of adverse reaction [see Dosage and Administration (2.3), Adverse Reactions (6.1)].

5.8 Hemorrhage

Hemorrhage can occur when MEKTOVI is administered in combination with encorafenib. In COLUMBUS, hemorrhage occurred in 19% of patients receiving MEKTOVI in combination with encorafenib. Grade 3 or greater hemorrhage occurred in 3.2% of patients. The most frequent hemorrhagic events were gastrointestinal, including rectal hemorrhage (4.2%), hematochezia (3.1%), and hemorrhoidal hemorrhage (1%). Fatal intracranial hemorrhage in the setting of new or progressive brain metastases occurred in 1.6% of patients.

In PHAROS, hemorrhage occurred in 12% of patients receiving MEKTOVI in combination with encorafenib including fatal hemorrhage intracranial (1%); Grade 3 or 4 hemorrhage occurred in 4.1% of patients. The most frequent hemorrhagic events were anal hemorrhage and hemothorax (2% each).

Withhold, reduce dose, or permanently discontinue based on severity of adverse reaction [see Dosage and Administration (2.3), Adverse Reactions (6.1)].

5.9 Embryo-Fetal Toxicity

Based on findings from animal studies and its mechanism of action, MEKTOVI can cause fetal harm when administered to a pregnant woman. Binimetinib was embryotoxic and abortifacient when administered to rabbits during the period of organogenesis at doses greater than or equal to those resulting in exposures approximately 5 times the human exposure at the recommended clinical dose of 45 mg twice daily.

Advise pregnant women and females of reproductive potential of the potential risk to a fetus. Advise females of reproductive potential to use effective contraception during treatment with MEKTOVI and for 30 days after the last dose [see Use in Specific Populations (8.1, 8.3)].

5.10 Risks Associated with Combination Treatment

MEKTOVI is indicated for use in combination with encorafenib. Refer to the encorafenib prescribing information for additional risk information that applies to combination use treatment.

6 ADVERSE REACTIONS

The following adverse reactions are described elsewhere in the labeling:

- New Primary Malignancies [see Warnings and Precautions (5.1)]
- Cardiomyopathy [see Warnings and Precautions (5.2)]
- Venous Thromboembolism [see Warnings and Precautions (5.3)]
- Ocular Toxicities [see Warnings and Precautions (5.4)]
- Interstitial Lung Disease [see Warnings and Precautions (5.5)]
- Hepatotoxicity [see Warnings and Precautions (5.6)]
- Rhabdomyolysis [see Warnings and Precautions (5.7)]
- Hemorrhage [see Warnings and Precautions (5.8)]
- Embryo-Fetal Toxicity [see Warnings and Precautions (5.9)]
- Risks Associated with Combination Treatment [see Warnings and Precautions (5.10)]

6.1 Clinical Trials Experience

Because clinical trials are conducted under widely varying conditions, adverse reaction rates observed in the clinical trials of a drug cannot be directly compared to rates in the clinical trials of another drug and may not reflect the rates observed in practice.

The data described in WARNINGS AND PRECAUTIONS reflect exposure of 192 patients with BRAF V600 mutation-positive unresectable or metastatic melanoma to MEKTOVI 45 mg twice daily in combination with encorafenib 450 mg once daily in a randomized open-label, active-controlled trial (COLUMBUS) [see Clinical Studies (14.1)] or, for rare events, exposure of 690 patients with BRAF V600 mutation-positive melanoma to MEKTOVI 45 mg twice daily in combination with encorafenib once daily across multiple clinical trials (NCT03915951, NCT01909453).

The pooled safety population described in the WARNINGS AND PRECAUTIONS also reflect exposure of 98 patients with BRAF V600E mutation-positive metastatic non-small cell lung cancer to MEKTOVI 45 mg twice daily and encorafenib 450 mg once daily until disease progression or unacceptable toxicity in PHAROS [see Clinical Studies (14.2)].

BRAF V600E or V600K Mutation-Positive Unresectable or Metastatic Melanoma

The data described below reflect exposure of 192 patients with BRAF V600 mutation-positive unresectable or metastatic melanoma to MEKTOVI (45 mg twice daily) in combination with encorafenib (450 mg once daily) in COLUMBUS.

The COLUMBUS trial [see Clinical Studies (14.1)] excluded patients with a history of Gilbert's syndrome, abnormal left ventricular ejection fraction, prolonged QTc (>480 msec), uncontrolled hypertension, and history or current evidence of retinal vein occlusion. The median duration of exposure was 11.8 months for patients treated with MEKTOVI in combination with encorafenib and 6.2 months for patients treated with vemurafenib.

The most common (≥25%) adverse reactions in patients receiving MEKTOVI in combination with encorafenib were fatigue, nausea, diarrhea, vomiting, and abdominal pain.

Adverse reactions leading to dose interruptions of MEKTOVI occurred in 33% of patients receiving MEKTOVI in combination with encorafenib; the most common were left ventricular dysfunction (6%) and serous retinopathy (5%). Adverse reactions leading to dose reductions of MEKTOVI occurred in 19% of patients receiving MEKTOVI in combination with encorafenib; the most common were left ventricular dysfunction (3%), serous retinopathy (3%), and colitis (2%). Five percent (5%) of patients receiving MEKTOVI in combination with encorafenib experienced an adverse reaction that resulted in permanent discontinuation of MEKTOVI. The most common adverse reactions resulting in permanent discontinuation of MEKTOVI were hemorrhage in 2% and headache in 1% of patients.

Table 3 and Table 4 present adverse drug reactions and laboratory abnormalities, respectively, identified in COLUMBUS. The COLUMBUS trial was not designed to demonstrate a statistically significant difference in adverse reaction rates for MEKTOVI in combination with encorafenib, as compared to vemurafenib, for any specific adverse reaction listed in Table 3.

Table 3: Adverse Reactions Occurring in ≥10% of Patients Receiving MEKTOVI in Combination with Encorafenib in COLUMBUS [Grades per National Cancer Institute CTCAE v4.03.]
Adverse Reaction | MEKTOVI with encorafenib N=192 |  | Vemurafenib N=186
Adverse Reaction | All Grades (%) | Grades 3 and 4 [Grade 4 adverse reactions limited to diarrhea (n=1) and hemorrhage (n=3) in the MEKTOVI with encorafenib arm and constipation (n=1) in the vemurafenib arm.] (%) | All Grades (%) | Grades 3 and 4 (%)
General Disorders and Administration Site Conditions
Fatigue [Represents a composite of multiple, related preferred terms.] | 43 | 3 | 46 | 6
Pyrexia | 18 | 4 | 30 | 0
Peripheral edema | 13 | 1 | 15 | 1
Gastrointestinal Disorders
Nausea | 41 | 2 | 34 | 2
Diarrhea | 36 | 3 | 34 | 2
Vomiting | 30 | 2 | 16 | 1
Abdominal pain | 28 | 4 | 16 | 1
Constipation | 22 | 0 | 6 | 1
Skin and Subcutaneous Tissue Disorders
Rash | 22 | 1 | 53 | 13
Nervous System Disorders
Dizziness | 15 | 3 | 4 | 0
Visual Disorders
Visual impairment | 20 | 0 | 4 | 0
Serous retinopathy/RPED | 20 | 3 | 2 | 0
Vascular Disorders
Hemorrhage | 19 | 3 | 9 | 2
Hypertension | 11 | 6 | 11 | 3

Other clinically important adverse reactions occurring in <10% of patients who received MEKTOVI in combination with encorafenib were:

Gastrointestinal disorders: Colitis

Skin and subcutaneous tissue disorders: Panniculitis, Photosensitivity

Immune system disorders: Drug hypersensitivity

Table 4: Laboratory Abnormalities Occurring in ≥10% (All grades) of Patients Receiving MEKTOVI in Combination with Encorafenib in COLUMBUS [Grades per National Cancer Institute CTCAE v4.03.]
Laboratory Abnormality | MEKTOVI with encorafenib N=192 |  | Vemurafenib N=186
Laboratory Abnormality | All Grades (%) | Grades 3 and 4 (%) | All Grades (%) | Grades 3 and 4 (%)
Hematology
Anemia | 36 | 3.6 | 34 | 2.2
Leukopenia | 13 | 0 | 10 | 0.5
Lymphopenia | 13 | 2.1 | 30 | 7
Neutropenia | 13 | 3.1 | 4.8 | 0.5
Chemistry
Increased Creatinine | 93 | 3.6 | 92 | 1.1
Increased Creatine Phosphokinase | 58 | 5 | 3.8 | 0
Increased Gamma Glutamyl Transferase | 45 | 11 | 34 | 4.8
Increased ALT | 29 | 6 | 27 | 2.2
Increased AST | 27 | 2.6 | 24 | 1.6
Increased Alkaline Phosphatase | 21 | 0.5 | 35 | 2.2
Hyponatremia | 18 | 3.6 | 15 | 0.5

BRAF V600E Mutation-Positive Metastatic Non-Small Cell Lung Cancer (NSCLC)

The safety of MEKTOVI in combination with encorafenib is described in 98 patients with BRAF V600E mutation-positive metastatic NSCLC who received MEKTOVI (45 mg twice daily) in combination with encorafenib (450 mg once daily) in an open-label, single-arm trial (PHAROS).

The PHAROS trial [see Clinical Studies (14.2)] excluded patients with abnormal LVEF, prolonged QTc (>480 ms), uncontrolled hypertension, and history or current evidence of retinal vein occlusion. The median duration of treatment for MEKTOVI and encorafenib was 8.4 and 9.2 months respectively.

The most common (≥25%) adverse reactions in patients receiving MEKTOVI were fatigue, nausea, diarrhea, musculoskeletal pain, vomiting, abdominal pain, visual impairment, constipation, dyspnea, rash, and cough.

Adverse reactions leading to dose interruptions of MEKTOVI occurred in 62% of patients receiving MEKTOVI; the most common (≥5%) were diarrhea (17%); nausea (15%); fatigue (9%); AST increased (7%); ALT increased, anemia, musculoskeletal pain, vomiting (6% each); and acute kidney injury, hemorrhage, and LV dysfunction/cardiomyopathy (5% each). Adverse reactions leading to dose reductions of MEKTOVI occurred in 33% of patients receiving MEKTOVI; the most common (≥5%) were diarrhea (8%), nausea (6%), and AST increased (5%). A total of 17% of patients receiving MEKTOVI experienced an adverse reaction that resulted in permanent discontinuation of MEKTOVI; the most common (≥2%) were diarrhea (3.1%); musculoskeletal pain, LV dysfunction/cardiomyopathy, fatigue, nausea, rash, visual impairment, and vomiting (2% each). None of the other adverse reactions leading to permanent discontinuation of MEKTOVI occurred in more than 1 patient.

Serious adverse reactions occurred in 38% of patients who received MEKTOVI in combination with encorafenib. Serious adverse reactions in ≥2% of patients included hemorrhage (6%); diarrhea (4.1%); anemia, dyspnea, pneumonia (3.1% each); arrhythmia, device related infection, edema, myocardial infarction, and pleural effusion (2% each). Fatal adverse reactions occurred in 2% of patients who received MEKTOVI (45 mg twice-daily) in combination with encorafenib, including intracranial hemorrhage and myocardial infarction (1% each).

Table 5 and Table 6 present adverse drug reactions and laboratory abnormalities, respectively, identified in PHAROS.

Table 5: Adverse Reactions Occurring in ≥10% of Patients Receiving MEKTOVI in Combination with Encorafenib in PHAROS [Grades per National Cancer Institute CTCAE v4.03.]
Adverse Reaction | MEKTOVI; with encorafenib; N=98
Adverse Reaction | All; Grades; (%) | Grade 3 and 4 [One Grade 5 adverse reaction of hemorrhage occurred.]; (%)
General Disorders and Administration Site Conditions
Fatigue [Fatigue includes fatigue, asthenia.] | 61 | 8
Edema [Edema includes edema peripheral, generalized edema, swelling, localized edema, face edema.] | 23 | 1
Pyrexia | 22 | 0
Gastrointestinal Disorders
Nausea | 58 | 3.1
Diarrhea [Diarrhea includes diarrhea, colitis.] | 52 | 7
Vomiting | 37 | 1
Abdominal pain [Abdominal pain includes abdominal pain, abdominal pain upper, abdominal discomfort, epigastric discomfort.] | 32 | 1
Constipation | 27 | 0
Eye Disorders
Visual impairment [Visual impairment includes vision blurred, visual impairment, vitreous floaters, photophobia, visual acuity reduced, photopsia.] | 29 | 2
Musculoskeletal and Connective Tissue Disorders
Musculoskeletal pain [Musculoskeletal pain includes back pain, arthralgia, pain in extremity, myalgia, musculoskeletal chest pain, non-cardiac chest pain, neck pain.] | 48 | 4.1
Skin and Subcutaneous Tissue Disorders
Rash [Rash includes rash, rash macular, rash maculo-papular, rash papular, rash pustular,dermatitis acneiform, palmar-plantar erythrodysesthesia syndrome, eczema, skin exfoliation.] | 27 | 3.1
Pruritis [Pruritis includes pruritus, pruritus genital.] | 16 | 0
Dry skin | 13 | 0
Alopecia | 12 | 0
Respiratory, Thoracic and Mediastinal Disorders
Dyspnea [Dyspnea includes dyspnea, dyspnea exertional.] | 27 | 8
Cough [Cough includes cough, productive cough.] | 26 | 0
Nervous System Disorders
Dizziness [Dizziness includes dizziness, balance disorder.] | 17 | 1
Headache | 11 | 0
Metabolism and Nutrition Disorders
Decreased appetite | 14 | 1
Vascular Disorders
Hemorrhage [Hemorrhage includes anal hemorrhage, hemothorax, gastrointestinal hemorrhage, hematochezia, hematuria, hemoptysis, hemorrhage intracranial, hyphema, small intestinal hemorrhage, upper gastrointestinal hemorrhage, vaginal hemorrhage.] | 12 | 4.1
Hypertension | 10 | 5
Cardiac Disorders
Left ventricular dysfunction/cardiomyopathy [Left ventricular dysfunction/cardiomyopathy includes ejection fraction decreased, cardiac failure, cardiac failure congestive.] | 11 | 1
Investigations
Weight increased | 11 | 1
Psychiatric Disorders
Insomnia | 10 | 0

Other clinically important adverse reactions occurring in <10% of patients who received MEKTOVI in combination with encorafenib were:

Nervous system disorders: Peripheral neuropathy, Dysgeusia, Facial paresis

Gastrointestinal disorders: Pancreatitis

Skin and subcutaneous tissue disorders: Hyperkeratosis, Erythema, Photosensitivity

Immune system disorders: Drug hypersensitivity

Table 6: Laboratory Abnormalities Occurring in ≥10% (All Grades) of Patients Receiving MEKTOVI with Encorafenib in PHAROS [Grades per National Cancer Institute CTCAE v4.03.]
Laboratory Abnormality [Based on the number of patients with available baseline and at least one on-treatment laboratory test.] | MEKTOVI with encorafenib
Laboratory Abnormality [Based on the number of patients with available baseline and at least one on-treatment laboratory test.] | All; Grades; (%) | Grades; 3 and 4; (%)
Hematology
Anemia | 47 | 11
Lymphopenia | 24 | 6
Thrombocytopenia | 20 | 1.1
Leukopenia | 12 | 0
Neutropenia | 12 | 1.1
Chemistry
Increased creatinine | 91 | 3.2
Hyperglycemia | 48 | 6
Increased creatine kinase | 41 | 3.3
Lipase increased | 40 | 14
Increased ALT | 34 | 9
Hypoalbuminemia | 32 | 0
Increased AST | 31 | 10
Increased alkaline phosphatase | 31 | 3.2
Hyperkalemia | 31 | 2.1
Hyponatremia | 26 | 11
Serum amylase increased | 22 | 1.1
Hypocalcemia | 12 | 2.1

7 DRUG INTERACTIONS

No clinically important drug interactions have been observed with MEKTOVI.

8 USE IN SPECIFIC POPULATIONS

8.1 Pregnancy

Risk Summary

Based on findings from animal reproduction studies and its mechanism of action [see Clinical Pharmacology (12.1)], MEKTOVI can cause fetal harm when administered to a pregnant woman. There are no available clinical data on the use of MEKTOVI during pregnancy. In animal reproduction studies, oral administration of binimetinib during the period of organogenesis was embryotoxic and an abortifacient in rabbits at doses greater than or equal to those resulting in exposures approximately 5 times the human exposure at the clinical dose of 45 mg twice daily (see Data). Advise pregnant women and females of reproductive potential of the potential risk to a fetus.

In the U.S. general population, the estimated background risk of major birth defects and miscarriage in clinically recognized pregnancies is 2% to 4% and 15% to 20%, respectively.

Data

Animal Data

In reproductive toxicity studies, administration of binimetinib to rats during the period of organogenesis resulted in maternal toxicity, decreased fetal weights and increased variations in ossification at doses ≥30 mg/kg/day (approximately 37 times the human exposure based on AUC at the recommended clinical dose of 45 mg twice daily). In pregnant rabbits, administration of binimetinib during the period of organogenesis resulted in maternal toxicity, decreased fetal body weights, an increase in malformations, and increased post-implantation loss, including total loss of pregnancy at doses ≥10 mg/kg/day (approximately 5 times the human exposure based on AUC at the recommended clinical dose of 45 mg twice daily). There was a significant increase in fetal ventricular septal defects and pulmonary trunk alterations at 20 mg/kg/day of binimetinib (less than 8 times the human exposure at the recommended clinical dose of 45 mg twice daily).

8.2 Lactation

Risk Summary

There are no data on the presence of binimetinib or its active metabolite in human milk, or the effects of binimetinib on the breastfed child, or the effects on milk production. Because of the potential for serious adverse reactions in a breastfed child, advise women not to breastfeed during treatment with MEKTOVI and for 3 days after the last dose.

8.3 Females and Males of Reproductive Potential

Based on animal data, MEKTOVI can cause fetal harm when administered to a pregnant woman [see Use in Specific Populations (8.1)].

Pregnancy Testing

Verify the pregnancy status of females of reproductive potential prior to initiating MEKTOVI [see Use in Specific Populations (8.1)].

Contraception

Females

Advise females of reproductive potential to use effective contraception during treatment with MEKTOVI and for 30 days after the last dose.

8.4 Pediatric Use

The safety and effectiveness of MEKTOVI have not been established in pediatric patients.

8.5 Geriatric Use

Of the 690 patients with BRAF mutation-positive melanoma who received MEKTOVI in combination with encorafenib across multiple clinical trials, 20% were aged 65 to 74 years and 8% were aged 75 years and older [see Clinical Pharmacology (12.3)].

Of the 98 patients with BRAF V600E mutation-positive metastatic NSCLC who received MEKTOVI in combination with encorafenib, 62 (63.2%) were 65 years of age and over and 20 (20.4%) were 75 years and over [see Clinical Studies (14.2)].

No overall differences in the safety or effectiveness of MEKTOVI plus encorafenib were observed in older patients as compared to younger patients.

8.6 Hepatic Impairment

Binimetinib concentrations may increase in patients with moderate or severe hepatic impairment. Dose adjustment for MEKTOVI is not recommended in patients with mild hepatic impairment (total bilirubin >1 and ≤1.5 × ULN and any AST or total bilirubin ≤ ULN and AST > ULN). Reduce the dose of MEKTOVI for patients with moderate (total bilirubin >1.5 and ≤3 × ULN and any AST) or severe (total bilirubin levels >3 × ULN and any AST) hepatic impairment [see Dosage and Administration (2.4), Clinical Pharmacology (12.3)].

10 OVERDOSAGE

Since binimetinib is 97% bound to plasma proteins, hemodialysis is likely to be ineffective in the treatment of overdose with MEKTOVI.

11 DESCRIPTION

Binimetinib is a kinase inhibitor. The chemical name is 5-[(4-bromo-2-fluorophenyl)amino]-4-fluoro-N-(2-hydroxyethoxy)-1-methyl-1H-benzimidazole-6-carboxamide. The molecular formula is C17H15BrF2N4O3 and the molecular weight is 441.2 daltons. The chemical structure of binimetinib is shown below:

Binimetinib is a white to slightly yellow powder. In aqueous media, binimetinib is slightly soluble at pH 1, very slightly soluble at pH 2, and practically insoluble at pH 4.5 and higher.

MEKTOVI (binimetinib) tablets for oral use contain 15 mg of binimetinib with the following inactive ingredients: lactose monohydrate, microcrystalline cellulose, croscarmellose sodium, magnesium stearate (vegetable source), and colloidal silicon dioxide. The coating contains polyvinyl alcohol, polyethylene glycol, titanium dioxide, talc, ferric oxide yellow, and ferrosoferric oxide.

12 CLINICAL PHARMACOLOGY

12.1 Mechanism of Action

Binimetinib is a reversible inhibitor of mitogen-activated extracellular signal regulated kinase 1 (MEK1) and MEK2 activity. MEK proteins are upstream regulators of the extracellular signal-related kinase (ERK) pathway. In vitro, binimetinib inhibited extracellular signal-related kinase (ERK) phosphorylation in cell-free assays as well as viability and MEK-dependent phosphorylation of BRAF-mutant human melanoma cell lines. Binimetinib also inhibited in vivo ERK phosphorylation and tumor growth in BRAF-mutant murine xenograft models.

Binimetinib and encorafenib target two different kinases in the RAS/RAF/MEK/ERK pathway. Compared to either drug alone, coadministration of encorafenib and binimetinib resulted in greater anti-proliferative activity in vitro in BRAF mutation-positive cell lines and greater anti-tumor activity with respect to tumor growth inhibition in BRAF V600E mutant human melanoma xenograft studies in mice. Additionally, the combination of binimetinib and encorafenib delayed the emergence of resistance in BRAF V600E mutant human melanoma xenografts in mice compared to either drug alone. In a BRAF V600E mutant NSCLC patient-derived xenograft model in mice, coadministration of encorafenib and binimetinib resulted in greater anti-tumor activity compared to binimetinib alone, with respect to tumor growth inhibition. Increased tumor growth delay after dosing cessation was also observed with the coadministration compared to either drug alone.

12.2 Pharmacodynamics

Cardiac Electrophysiology

Following MEKTOVI 45 mg twice daily, no clinically meaningful QT prolongation was observed.

12.3 Pharmacokinetics

The pharmacokinetics of binimetinib was studied in healthy subjects and patients with solid tumors. After twice-daily dosing, the accumulation is 1.5-fold and the coefficient of variation (CV%) of the area under the concentration-time curve (AUC) is <40% at steady state. The systemic exposure of binimetinib is approximately dose proportional.

Absorption

After oral administration, at least 50% of the binimetinib dose was absorbed with a median time to maximum concentration (Tmax) of 1.6 hours.

Effect of Food

The administration of a single dose of MEKTOVI 45 mg with a high-fat, high-calorie meal (consisting of approximately 150 calories from protein, 350 calories from carbohydrate, and 500 calories from fat) in healthy subjects had no effect on binimetinib exposure.

Distribution

Binimetinib is 97% bound to human plasma proteins and the blood-to-plasma ratio is 0.72. The geometric mean (CV%) of apparent volume of distribution of binimetinib is 92 L (45%).

Elimination

The mean (CV%) terminal half-life (t1/2) of binimetinib is 3.5 hours (28.5%) and apparent clearance (CL/F) is 20.2 L/h (24%).

Metabolism

The primary metabolic pathway is glucuronidation with UGT1A1 contributing up to 61% of the binimetinib metabolism. Other pathways of binimetinib metabolism include N-dealkylation, amide hydrolysis, and loss of ethane-diol from the side chain. The active metabolite M3 produced by CYP1A2 and CYP2C19 represents 8.6% of the binimetinib exposure. Following a single oral dose of 45 mg radiolabeled binimetinib, approximately 60% of the circulating radioactivity AUC in plasma was attributable to binimetinib.

Excretion

Following a single oral dose of 45 mg radiolabeled binimetinib in healthy subjects, 62% (32% unchanged) of the administered dose was recovered in the feces while 31% (6.5% unchanged) was recovered in the urine.

Specific Populations

Age (20 to 94 years), sex, or body weight do not have a clinically important effect on the systemic exposure of binimetinib. The effect of race or ethnicity on the pharmacokinetics of binimetinib is unknown.

Hepatic Impairment: No clinically meaningful changes in binimetinib exposure (AUC and Cmax) were observed in subjects with mild hepatic impairment (total bilirubin >1 and ≤1.5 × ULN and any AST or total bilirubin ≤ ULN and AST > ULN) as compared to subjects with normal liver function (total bilirubin ≤ ULN and AST ≤ ULN). A 2-fold increase in AUC was observed in subjects with moderate (total bilirubin >1.5 and ≤3 × ULN and any AST) or severe (total bilirubin levels >3 × ULN and any AST) hepatic impairment [see Dosage and Administration (2.4)].

Renal Impairment: In subjects with severe renal impairment (eGFR ≤29 mL/min/1.73 m^2), no clinically important changes in binimetinib exposure were observed as compared to subjects with normal renal function.

Drug Interaction Studies

Clinical Studies

Effect of UGT1A1 Inducers or Inhibitors on Binimetinib: UGT1A1 genotype and smoking (UGT1A1 inducer) do not have a clinically important effect on binimetinib exposure. Simulations predict similar Cmax of binimetinib 45 mg in the presence or absence of atazanavir 400 mg (UGT1A1 inhibitor).

No differences in binimetinib exposure have been observed when MEKTOVI is coadministered with encorafenib.

Effect of Binimetinib on CYP Substrates: Binimetinib did not alter the exposure of a sensitive CYP3A4 substrate (midazolam).

Effect of Acid Reducing Agents on Binimetinib: The extent of binimetinib exposure (AUC) was not altered in the presence of a gastric acid reducing agent (rabeprazole).

In Vitro Studies

Effect of Binimetinib on CYP Substrates: Binimetinib is not a time-dependent inhibitor of CYP1A2, CYP2C9, CYP2D6 or CYP3A.

Effect of Transporters on Binimetinib: Binimetinib is a substrate of P-glycoprotein (P-gp) and breast cancer resistance protein (BCRP). Binimetinib is not a substrate of organic anion transporting polypeptide (OATP1B1, OATP1B3, OATP2B1) or organic cation transporter 1 (OCT1).

13 NONCLINICAL TOXICOLOGY

13.1 Carcinogenesis, Mutagenesis, Impairment of Fertility

Carcinogenicity studies with binimetinib have not been conducted. Binimetinib was not genotoxic in studies evaluating reverse mutations in bacteria, chromosomal aberrations in mammalian cells, or micronuclei in bone marrow of rats.

No dedicated fertility studies have been conducted with binimetinib in animals. In general toxicology studies in rats and monkeys, there were no remarkable findings in male or female reproductive organs.

14 CLINICAL STUDIES

14.1 BRAF V600E or V600K Mutation-Positive Unresectable or Metastatic Melanoma

MEKTOVI in combination with encorafenib was evaluated in a randomized, active-controlled, open-label, multicenter trial (COLUMBUS; NCT01909453). Eligible patients were required to have BRAF V600E or V600K mutation-positive unresectable or metastatic melanoma, as detected using the bioMerieux THxID™BRAF assay. Patients were permitted to have received immunotherapy in the adjuvant setting and one prior line of immunotherapy for unresectable locally advanced or metastatic disease. Prior use of BRAF inhibitors or MEK inhibitors was prohibited. Randomization was stratified by American Joint Committee on Cancer (AJCC) Stage (IIIB, IIIC, IVM1a or IVM1b, versus IVM1c), Eastern Cooperative Oncology Group (ECOG) performance status (0 versus 1), and prior immunotherapy for unresectable or metastatic disease (yes versus no).

Patients were randomized (1:1:1) to receive MEKTOVI 45 mg twice daily in combination with encorafenib 450 mg once daily (MEKTOVI in combination with encorafenib), encorafenib 300 mg once daily, or vemurafenib 960 mg twice daily. Treatment continued until disease progression or unacceptable toxicity. Only the results of the approved dosing (MEKTOVI 45 mg in combination with encorafenib 450 mg) are described below.

The major efficacy outcome measure was progression-free survival (PFS), as assessed by a blinded independent central review, to compare MEKTOVI in combination with encorafenib with vemurafenib. Additional efficacy measures included overall survival (OS), as well as objective response rate (ORR) and duration of response (DoR) which were assessed by central review.

A total of 577 patients were randomized, 192 to the MEKTOVI in combination with encorafenib arm, 194 to the encorafenib arm, and 191 to the vemurafenib arm. Of the 383 patients randomized to either the MEKTOVI in combination with encorafenib or the vemurafenib arms, the median age was 56 years (20 to 89 years), 59% were male, 91% were White, and 72% had baseline ECOG performance status of 0. Ninety-five percent (95%) had metastatic disease, 65% were Stage IVM1c, and 4% received prior CTLA-4, PD-1, or PD-L1 directed antibodies. Twenty-eight percent (28%) had elevated baseline serum lactate dehydrogenase (LDH), 45% had ≥3 organs with tumor involvement at baseline, and 3% had brain metastases. Based on centralized testing, 100% of patients’ tumors tested positive for BRAF mutations; BRAF V600E (88%), BRAF V600K (11%), or both (<1%).

MEKTOVI in combination with encorafenib demonstrated a statistically significant improvement in PFS compared to vemurafenib. Efficacy results are summarized in Table 7 and Figure 1.

Table 7: Efficacy Results for COLUMBUS
 | MEKTOVI; with encorafenib; N=192 | Vemurafenib; N=191
Progression-Free Survival
Number of events (%) | 98 (51) | 106 (55)
Progressive disease | 88 (46) | 104 (54)
Death | 10 (5) | 2 (1)
Median PFS, months (95% CI) | 14.9 (11.0, 18.5) | 7.3 (5.6, 8.2)
HR (95% CI) [Estimated with Cox proportional hazard model adjusted by the following stratification factors: American Joint Committee on Cancer (AJCC) Stage (IIIB, IIIC, IVM1a or IVM1b, versus IVM1c) and Eastern Cooperative Oncology Group (ECOG) performance status (0 versus 1).] | 0.54 (0.41, 0.71)
P value [Log-rank test adjusted by the same stratification factors.] | <0.0001
Overall Survival [Based on a cutoff date 82.4 months after the date of PFS analysis.]
Number of events (%) | 139 (72) | 147 (77)
Median OS, months (95% CI) | 33.6 (24.4, 39.2) | 16.9 (14.0, 24.5)
HR (95% CI) | 0.67 (0.53, 0.84)
Overall Response Rate
ORR (95% CI) | 63% (56%, 70%) | 40% (33%, 48%)
CR | 8% | 6%
PR | 55% | 35%
Duration of Response
Median DoR, months (95% CI) | 16.6 (12.2, 20.4) | 12.3 (6.9, 16.9)
CI = Confidence interval; CR = Complete response; DoR = Duration of response; HR = Hazard ratio; NE = Not estimable; ORR = Overall response rate; OS = Overall survival; PFS = Progression-free survival; PR = Partial response.

Figure 1: Kaplan-Meier Curves for Progression-Free Survival in COLUMBUS

14.2 BRAF V600E Mutation-Positive Metastatic Non-Small Cell Lung Cancer

MEKTOVI in combination with encorafenib was evaluated in an open-label, multicenter, single-arm study in patients with BRAF V600E mutation-positive metastatic non-small cell lung cancer (NSCLC) (PHAROS; NCT03915951). Eligible patients had a diagnosis of histologically-confirmed metastatic NSCLC with BRAF V600E mutation that was treatment-naïve or had been previously treated with 1 prior line of systemic therapy in the metastatic setting (platinum-based chemotherapy and/or anti-PD-1/PD-L1 therapies), age 18 years or older, Eastern Cooperative Oncology Group (ECOG) performance status (PS) of 0 or 1, and measurable disease as defined by Response Evaluation Criteria in Solid Tumors (RECIST) v1.1. Prior use of BRAF inhibitors or MEK inhibitors was not allowed.

Patients received MEKTOVI 45 mg orally twice daily and encorafenib 450 mg once daily until disease progression or unacceptable toxicity. The major efficacy outcome measures were objective response rate (ORR) per RECIST v1.1 and duration of response (DoR) as assessed by independent review committee (IRC).

In the efficacy population, BRAF V600E mutation status was determined by prospective local testing using tumor tissue (78%) or blood (22%) specimens. Of the 98 patients with BRAF V600E mutation, 6 patients were enrolled into the trial based on testing of their tumor tissue specimens with the FoundationOne CDx tissue test. Of the remaining 92 patients enrolled based on local testing, 68 patients had their tumor tissue specimens retrospectively confirmed as having BRAF V600E positive status by the FoundationOne CDx tissue test. The remaining patients had either BRAF V600E negative status (n=5) or had unevaluable results (n=19) by the FoundationOne CDx tissue test. In addition, plasma samples from 81 out of 98 patients were retrospectively tested using the FoundationOne Liquid CDx assay. Of the 81 patients, 48 were confirmed positive for BRAF V600E, while 33 patients were BRAF V600E mutation negative by FoundationOne Liquid CDx assay. The remaining 17 samples had unevaluable results with FoundationOne Liquid CDx assay.

The efficacy population included 59 treatment-naïve patients and 39 previously-treated patients. Among these 98 patients, the median age was 70 years (range: 47 to 86); 53% female; 88% White, 7% Asian, 3% Black or African American, and 1% American Indian or Alaska Native; 99% were not Hispanic or Latino; 13% were current smokers and 57% were former smokers; 73% had ECOG PS of 1; and 97% had adenocarcinoma. All patients had metastatic disease and 8% had brain metastases at baseline.

Efficacy results for patients with BRAF V600E mutation-positive metastatic NSCLC are summarized in Table 8.

Table 8: Efficacy Results for PHAROS
 | MEKTOVI with encorafenib
Efficacy Parameter | Treatment naïve; (N=59) | Previously treated; (N=39)
Objective Response Rate [Assessed by Independent Central Review (ICR).]
ORR (95% CI) | 75% (62, 85) | 46% (30, 63)
CR | 15% | 10%
PR | 59% | 36%
Duration of Response [Based on observed duration of response.] | N=44 | N=18
Range in months | 1.4, 51.6+ | 3.8, 45.8+
% with DoR ≥12 months | 64% | 44%
% with DoR ≥24 months | 43% | 22%
CI = Confidence interval; CR = Complete response; DoR = Duration of response; N = Number of patients; NE = Not estimable; ORR = Objective response rate; PR = Partial response.

16 HOW SUPPLIED/STORAGE AND HANDLING

MEKTOVI (binimetinib) is supplied as 15 mg yellow/dark yellow, unscored biconvex oval film-coated tablets debossed with a stylized "A" on one side and "15" on the other side, available in bottles of 180 tablets (NDC 70255-010-02).

STORAGE AND HANDLING

Store at 20°C to 25°C (68°F to 77°F); excursions permitted between 15°C and 30°C (59°F and 86°F) [see USP Controlled Room Temperature].

17 PATIENT COUNSELING INFORMATION

Advise the patient to read the FDA-approved patient labeling (Medication Guide).

Inform patients of the following:

New Primary Malignancies

Advise patients that MEKTOVI administered with encorafenib can result in the development of new primary cutaneous and non-cutaneous malignancies. Advise patients to contact their healthcare provider immediately for any new lesions, changes to existing lesions on their skin, or other signs and symptoms of malignancies [see Warnings and Precautions (5.1)].

Cardiomyopathy

Advise patients to report any symptoms of heart failure to their healthcare provider [see Warnings and Precautions (5.2)].

Venous Thromboembolism

Advise patients to contact their healthcare provider if they experience symptoms of venous thrombosis or pulmonary embolism. Advise patients to seek medical attention for sudden onset of difficulty breathing, leg pain, or swelling [see Warnings and Precautions (5.3)].

Ocular Toxicities

Advise patients to contact their healthcare provider as soon as possible if they experience any changes in their vision [see Warnings and Precautions (5.4)].

Interstitial Lung Disease

Advise patients to contact their healthcare provider if they experience any new or worsening respiratory symptoms including cough or dyspnea [see Warnings and Precautions (5.5)].

Hepatotoxicity

Advise patients that serial testing of serum liver tests (ALT, AST, bilirubin) is recommended during treatment with MEKTOVI. Instruct patients to report symptoms of liver dysfunction including jaundice, dark urine, nausea, vomiting, loss of appetite, fatigue, bruising, or bleeding [see Warnings and Precautions (5.6)].

Rhabdomyolysis

Advise patients to contact their healthcare provider as soon as possible if they experience unusual or new onset weakness, myalgia, or darkened urine [see Warnings and Precautions (5.7)].

Hemorrhage

Advise patients to notify their healthcare provider if they experience symptoms suggestive of hemorrhage, such as unusual bleeding [see Warnings and Precautions (5.8)].

Females and Males of Reproductive Potential

Embryo-Fetal Toxicity: Advise females with reproductive potential of the potential risk to a fetus. Advise females to contact their healthcare provider if they become pregnant, or if pregnancy is suspected, during treatment with MEKTOVI [see Warnings and Precautions (5.9), Use in Specific Populations (8.1)]. Advise females of reproductive potential to use effective contraception during treatment with MEKTOVI and for 30 days after the last dose.

Lactation: Advise women not to breastfeed during treatment with MEKTOVI and for 3 days after the last dose [see Use in Specific Populations (8.2)].

Distributed by:
Array BioPharma Inc., a wholly owned subsidiary of Pfizer Inc.
3200 Walnut Street
Boulder, CO 80301

© 2023 Array BioPharma Inc. All rights reserved.
MEKTOVI® is a registered trademark of Array BioPharma Inc. in the United States and various other countries.

This product’s labeling may have been updated. For the most recent Prescribing Information, please visit www.pfizer.com.

LAB-1426-4.0

MEDICATION GUIDE

MEKTOVI® (mek-TOE-vee)

(binimetinib)

tablets

Important Information: If your healthcare provider prescribes MEKTOVI with encorafenib, please read the Medication Guide that comes with encorafenib.

What is the most important information I should know about MEKTOVI when taken in combination with encorafenib?

MEKTOVI when taken in combination with encorafenib may cause serious side effects, including:

- Risk of new skin cancers. MEKTOVI, when used with encorafenib, may cause skin cancers called cutaneous squamous cell carcinoma or basal cell carcinoma.
Talk to your healthcare provider about your risk for these cancers.
Check your skin and tell your healthcare provider right away about any skin changes, including a:
  1. new wart
  2. skin sore or reddish bump that bleeds or does not heal
  3. change in size or color of a mole
Your healthcare provider should check your skin before treatment with MEKTOVI, when taken in combination with encorafenib, every 2 months during treatment, and for up to 6 months after you stop treatment to look for any new skin cancers.
Your healthcare provider should also check for cancers that may not occur on the skin. Tell your healthcare provider about any new symptoms that develop during treatment with MEKTOVI when taken in combination with encorafenib.

See "What are the possible side effects of MEKTOVI?" for more information about side effects.

What is MEKTOVI?

MEKTOVI is a prescription medicine used:

- in combination with a medicine called encorafenib to treat people with a type of skin cancer called melanoma:
  - that has spread to other parts of the body or cannot be removed by surgery, and
  - that has a certain type of abnormal “BRAF” gene
- in combination with a medicine called encorafenib to treat adults with a type of lung cancer called non-small cell lung cancer (NSCLC):
  - that has spread to other parts of the body, and
  - that has a certain type of abnormal “BRAF” gene

Your healthcare provider will perform a test to make sure that MEKTOVI is right for you.

It is not known if MEKTOVI is safe and effective in children.

Before taking MEKTOVI, tell your healthcare provider about all of your medical conditions, including if you:

- have heart problems
- have had blood clots
- have eye problems
- have lung or breathing problems
- have liver or kidney problems
- have any muscle problems
- have bleeding problems
- have high blood pressure (hypertension)
- are pregnant or plan to become pregnant. MEKTOVI can harm your unborn baby.
  - Females who are able to become pregnant should use effective birth control (contraception) during treatment with MEKTOVI and for at least 30 days after the last dose of MEKTOVI.
  - Talk to your healthcare provider about birth control methods that may be right for you during this time.
  - Your healthcare provider will do a pregnancy test before you start taking MEKTOVI. Tell your healthcare provider right away if you become pregnant or think you might be pregnant during treatment with MEKTOVI.
- are breastfeeding or plan to breastfeed. It is not known if MEKTOVI passes into your breast milk. Do not breastfeed during treatment with MEKTOVI and for 3 days after the last dose of MEKTOVI. Talk to your healthcare provider about the best way to feed your baby during this time.

Tell your healthcare provider about all the medicines you take, including prescription and over-the-counter medicines, vitamins, and herbal supplements.

Know the medicines you take. Keep a list of them to show your healthcare provider and pharmacist when you get a new medicine.

How should I take MEKTOVI?

- Take MEKTOVI exactly as your healthcare provider tells you to take it. Do not change your dose or stop taking MEKTOVI unless your healthcare provider tells you to.
- Take MEKTOVI in combination with encorafenib by mouth 2 times a day, about 12 hours apart.
- MEKTOVI may be taken with or without food.
- If you miss a dose of MEKTOVI, take it as soon as you remember. If it is within 6 hours of your next scheduled dose, take your next dose at your regular time. Do not make up for the missed dose.
- Do not take an extra dose if you vomit after taking your scheduled dose. Take your next dose at your regular time.
- If you stop treatment with encorafenib, talk to your healthcare provider about whether your MEKTOVI treatment may need to be stopped.

What are the possible side effects of MEKTOVI?

MEKTOVI may cause serious side effects, including:

- Heart problems, including heart failure. MEKTOVI, when taken with encorafenib, can cause heart problems. Your healthcare provider should check your heart function before and during treatment with MEKTOVI. Call your healthcare provider right away if you have any of the following signs and symptoms of a heart problem:
  - feeling like your heart is pounding or racing
  - shortness of breath
  - swelling of your ankles and feet
  - feeling lightheaded
- Blood clots. MEKTOVI, when taken with encorafenib, can cause blood clots in your arms or legs, which can travel to your lungs and can lead to death. Get medical help right away if you have the following symptoms:
  - chest pain
  - sudden shortness of breath or trouble breathing
  - pain in your legs with or without swelling
  - swelling in your arms and legs
  - a cool pale arm or leg
- Eye problems. MEKTOVI, when taken with encorafenib, can cause eye problems. Your healthcare provider should perform an eye exam regularly during treatment with MEKTOVI. Tell your healthcare provider right away if you develop any new or worsening symptoms of eye problems, including:
  - blurred vision, loss of vision, or other vision changes
  - see colored dots
  - see halos (blurred outline around objects)
  - eye pain, swelling, or redness
- Lung or breathing problems. MEKTOVI, when taken with encorafenib, can cause lung or breathing problems. Tell your healthcare provider if you have any new or worsening symptoms of lung or breathing problems, including:
  - shortness of breath
  - cough
- Liver problems. MEKTOVI, when taken with encorafenib, can cause liver problems. Your healthcare provider should perform blood tests to check your liver function before and during treatment with MEKTOVI. Tell your healthcare provider if you have any of the following signs and symptoms of a liver problem:

- yellowing of your skin or your eyes
- dark or brown (tea-colored) urine
- nausea or vomiting
- loss of appetite

- tiredness
- bruising
- bleeding

- Muscle problems (rhabdomyolysis). MEKTOVI, when taken with encorafenib, can cause muscle problems that can be severe. Treatment with MEKTOVI may increase the level of an enzyme in your blood called creatine phosphokinase (CPK) and can be a sign of muscle damage. Your healthcare provider should perform a blood test to check your levels of CPK before and during treatment. Tell your healthcare provider right away if you develop any of these symptoms:
  - weakness
  - muscle aches or pain
  - dark, reddish urine
- Bleeding problems. MEKTOVI, when taken with encorafenib, can cause serious bleeding problems, including in your brain or stomach, that can lead to death. Tell your healthcare provider and get medical help right away if you develop any signs of bleeding, including:
  - headaches, dizziness, or feeling weak
  - cough up blood or blood clots
  - vomit blood or your vomit looks like “coffee grounds”
  - red or black stool that look like tar

Your healthcare provider may change your dose, temporarily stop, or permanently stop treatment with MEKTOVI if you have certain side effects.

The most common side effects of MEKTOVI when taken with encorafenib for melanoma include:

- fatigue
- nausea
- diarrhea

- vomiting
- stomach-area (abdominal) pain

The most common side effects of MEKTOVI when taken with encorafenib for NSCLC include:

- fatigue
- nausea
- diarrhea
- muscle or joint pain
- vomiting
- stomach-area (abdominal) pain

- blurred vision, loss of vision, or other vision changes
- constipation
- shortness of breath
- rash
- cough

These are not all of the possible side effects of MEKTOVI.

Call your doctor for medical advice about side effects. You may report side effects to FDA at 1-800-FDA-1088.

You may also report side effects to Pfizer Inc. at 1-800-438-1985.

How should I store MEKTOVI?

- Store MEKTOVI at room temperature between 68°F to 77°F (20°C to 25°C).

Keep MEKTOVI and all medicines out of the reach of children.

General information about the safe and effective use of MEKTOVI.

Medicines are sometimes prescribed for purposes other than those listed in a Medication Guide. Do not use MEKTOVI for a condition for which it was not prescribed. Do not give MEKTOVI to other people, even if they have the same symptoms that you have. It may harm them. You can ask your healthcare provider or pharmacist for information about MEKTOVI that is written for health professionals.

What are the ingredients in MEKTOVI?

Active ingredient: binimetinib

Inactive ingredients: lactose monohydrate, microcrystalline cellulose, croscarmellose sodium, magnesium stearate (vegetable source), and colloidal silicon dioxide

Tablet coating: polyvinyl alcohol, polyethylene glycol, titanium dioxide, talc, ferric oxide yellow, ferrosoferric oxide

Distributed by: Array BioPharma Inc., a wholly owned subsidiary of Pfizer Inc., Boulder, Colorado 80301.

MEKTOVI® is a registered trademark of Array BioPharma Inc. in the United States and various other countries.

For more information, go to www.BRAFTOVIMEKTOVI.com or call 1-844-792-7729.

©2020 Array BioPharma Inc. All rights reserved.

LAB-1427-2.0

This Medication Guide has been approved by the U.S. Food and Drug Administration.
Revised: 10/2023

PRINCIPAL DISPLAY PANEL - 15 mg Tablet Bottle Label

NDC 70255-010-02

MEKTOVI®
(binimetinib) tablets

15 mg

Rx only

180 Tablets

PRINCIPAL DISPLAY PANEL - 15 mg Tablet Bottle Carton

NDC 70255-010-02

MEKTOVI®
(binimetinib) tablets

15 mg

Rx only

180 Tablets